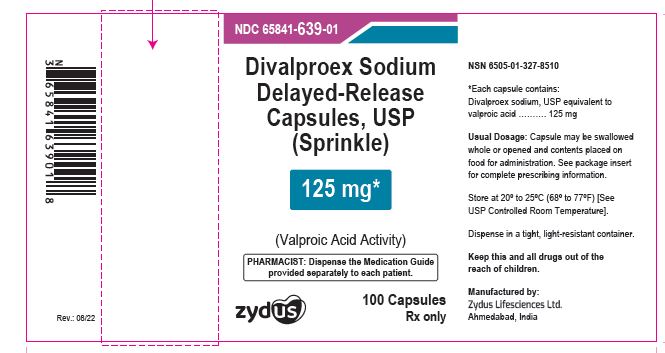 DRUG LABEL: divalproex sodium
NDC: 65841-639 | Form: CAPSULE, COATED PELLETS
Manufacturer: Zydus Lifesciences Limited
Category: prescription | Type: HUMAN PRESCRIPTION DRUG LABEL
Date: 20241128

ACTIVE INGREDIENTS: DIVALPROEX SODIUM 125 mg/1 1
INACTIVE INGREDIENTS: ALCOHOL; AMMONIA; BUTYL ALCOHOL; CELLULOSE, MICROCRYSTALLINE; FD&C BLUE NO. 1; FERROSOFERRIC OXIDE; GELATIN; HYPROMELLOSES; ISOPROPYL ALCOHOL; METHACRYLIC ACID; POTASSIUM HYDROXIDE; PROPYLENE GLYCOL; SHELLAC; SILICON DIOXIDE; SODIUM LAURYL SULFATE; TALC; TITANIUM DIOXIDE; TRIETHYL CITRATE; WATER

DIVALPROEX SODIUM DELAYED-RELEASE CAPSULES

PACKAGE LABEL.PRINCIPAL DISPLAY PANEL

NDC 65841-639-01 in bottle of 100 Capsules

Divalproex sodium delayed-release capsules, USP (sprinkle)

Rx only

100 capsules